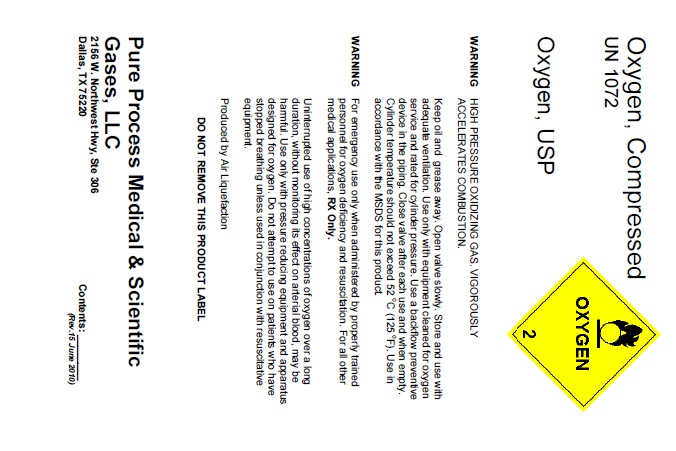 DRUG LABEL: Oxygen
NDC: 51051-001 | Form: GAS
Manufacturer: Pure Process Medical & Scientific Gases, LLC
Category: prescription | Type: HUMAN PRESCRIPTION DRUG LABEL
Date: 20100623

ACTIVE INGREDIENTS: Oxygen 990 mL/1 L

oxygen

PACKAGE LABEL

Oxygen, Compressed
UN 1072
OXYGEN 2
Oxygen, USP
WARNING HIGH PRESSURE OXIDIZING GAS. VIGOROUSLY ACCELERATES COMBUSTION.
Keep oil and grease away. Open valve slowly. Store and use with adequate ventilation. Use only with equipment cleaned for oxygen service and rated for cylinder pressure. Use a backflow preventive device in the piping. Close valve after each use and when empty. Cylinder temperature should not exceed 52 oC (125 oF). Use in accordance with the MSDS for this product.
WARNING For emergency use only when administered by properly trained personnel for oxygen deficiency and resuscitation. For all other medical applications, RX Only.
Uninterrupted use of high concentrations of oxygen over a long duration, without monitoring its effect on arterial blood, may be harmful. Use only with pressure reducing equipment and apparatus designed for oxygen. Do not attempt to use on patients who have stopped breathing unless used in conjunction with resuscitative equipment.
Produced by Air Liquefaction
DO NOT REMOVE THIS PRODUCT LABEL
Pure Process Medical and Scientific Gases, LLC
2156 W. Northwest Hwy, Ste 306
Dallas, TX 75220 Contents: ________
(Rev.15 June 2010)